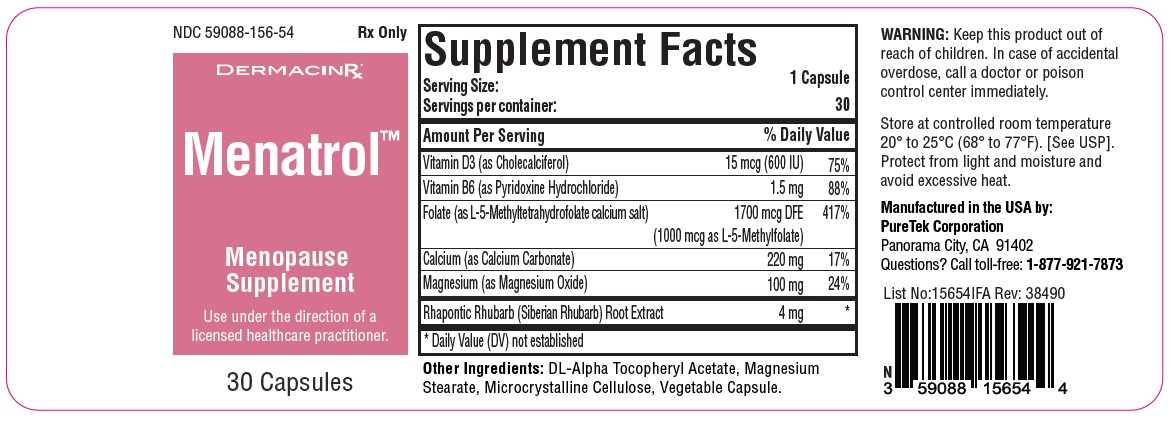 DRUG LABEL: Menatrol
NDC: 59088-156 | Form: CAPSULE
Manufacturer: PureTek Corporation
Category: prescription | Type: HUMAN PRESCRIPTION DRUG LABEL
Date: 20231218

ACTIVE INGREDIENTS: PYRIDOXINE HYDROCHLORIDE 1.5 mg/1 1; CHOLECALCIFEROL 600 [iU]/1 1; LEVOMEFOLATE CALCIUM 1000 ug/1 1; MAGNESIUM OXIDE 100 mg/1 1; RHUBARB 4 mg/1 1; CALCIUM CARBONATE 220 mg/1 1
INACTIVE INGREDIENTS: .ALPHA.-TOCOPHEROL ACETATE, DL-; CELLULOSE, MICROCRYSTALLINE; MAGNESIUM STEARATE

Menatrol

DESCRIPTION:

Full Prescribing Information:
Drug Description:
Menatrol™ Capsules are a comprehensive dietary supplement tailored for individuals undergoing menopause. This specialized formulation offers a blend of vitamins, minerals, and plant extracts aiming to alleviate common menopausal symptoms:

Vitamin D3 (Cholecalciferol): Contained in a dose of 15 mcg (600 IU), Vitamin D3 plays a pivotal role in maintaining bone health and may also help mitigate mood disturbances. It is recommended to seek a supplement offering 600-800 IU of Vitamin D3 daily, although personal dosing should be discussed with a licensed healthcare practitioner.
Vitamin B6 (Pyridoxine Hydrochloride): At a dosage of 1.5 mg, Vitamin B6 is integral for mood stabilization and promoting energy. Typically, adults are advised to consume 1.3-2.0 mg per day. Always refer to the supplement label for specific dosages.
Folate (L-5-Methyltetrahydrofolate calcium salt): Provided in a measure of 1700 mcg DFE (with 1000 mcg as L-5-Methylfolate), folate is pivotal for holistic health, potentially aiding in mood enhancement and energy regulation. An average adult dosage is between 400-800 mcg daily.
Calcium (Calcium Carbonate): At a concentration of 220 mg, calcium is a key mineral that fortifies bones, particularly crucial during menopause due to heightened osteoporosis risks. Women over 50 typically require around 1000-1300 mg of calcium daily, although intake should be calibrated based on diet.
Magnesium (Magnesium Oxide): Present in an amount of 100 mg, magnesium offers relief from muscle cramps, mood fluctuations, and sleep disturbances. On average, adults are recommended to consume 300-400 mg per day, though individual requirements can differ.
Rhapontic Rhubarb: Rhapontic rhubarb (Rheum rhaponticum) is a natural ingredient that some women use to address menopausal symptoms, including hot flashes and mood swings. The appropriate dosage for this specific ingredient may vary, so consult the product label or a licensed healthcare practitioner for guidance.

Each capsule contains:
Vitamin D3 (as Cholecalciferol)....................................15 mcg (600 IU)
Vitamin B6 (as Pyridoxine Hydrochloride)....................1.5 mg
Folate (as L-5-Methyltetrahydrofolate calcium salt)......1700 mcg DFE (1000 mcg as L-5-Methylfolate)
Calcium (as Calcium Carbonate)..................................220 mg
Magnesium (as Magnesium Oxide)..............................100 mg
Rhapontic Rhubarb (Siberian Rhubarb) Root Extract...4 mg

Other Ingredients:

DL-Alpha Tocopheryl Acetate, Magnesium Stearate, Microcrystalline Cellulose, Vegetable Capsule.

Indications and Usage:

For the dietary management of menopausal symptoms and the support of overall health during the menopausal phase.

Contraindications:

This product is contraindicated in patients with a known hypersensitivity to any of the ingredients. Menatrol™ Capsules are contraindicated in patients with hypercalcemia, malabsorption syndrome, abnormal sensitivity to the toxic effects of vitamin D, and hypervitaminosis D.

Warnings:

Tell your doctor if you have: kidney problems, thyroid disease. This medication should be used as directed during pregnancy or while breast-feeding. Consult your doctor. Administration of folate alone is improper therapy for pernicious anemia and other megaloblastic anemias in which vitamin B12 is deficient.

Precautions

Folate in doses above 0.1 mg daily may obscure pernicious anemia, in that hematologic remission can occur while neurological manifestations remain progressive. There is a potential danger in administering folate to patients with undiagnosed anemia, since folate may obscure the diagnosis of pernicious anemia by alleviating the hematologic manifestations of the disease while allowing the neurologic complications to progress. This may result in severe nervous system damage before the correct diagnosis is made. The patient’s medical conditions and consumption of other drugs, herbs, and/or supplements should be considered.

Adverse Reactions:

Possible side effects may include gastrointestinal upset. If any side effects persist or worsen, discontinue use and consult a physician.

Drug Interactions:

Consult with a licensed healthcare practitioner before use if taking prescription medications, especially those affecting bone health or hormonal therapies.

Pregnancy and Lactation:

Not recommended for use during pregnancy or lactation without consulting with a licensed healthcare practitioner.

Overdosage:

In case of overdose, seek medical attention immediately. Symptoms may include nausea, vomiting, or diarrhea.

Clinical Pharmacology:

The ingredients in this formulation work synergistically to potentially alleviate various menopausal symptoms by supporting bone health, mood regulation, and overall wellness.

Nonclinical Toxicology:

There are no known toxicities associated with the recommended doses of the ingredients in this supplement.

Clinical Studies:

Several ingredients in this supplement have been clinically studied for their effectiveness in managing menopausal symptoms, including bone health, mood disturbances, and overall well-being.

Dosage and Administration:

Take one (1) capsule daily or as directed by a licensed healthcare practitioner.

How Supplied:

Menatrol™ Capsules are light yellow powder with black specks, encased in a hard shell capsule. They are packaged in bottle containing 30 capsules – NDC 59088-156-54. Dispense in a tight, light-resistant container as defined in the USP/NF with a child resistant closure.

Storage

Do not use if bottle seal is broken.
KEEP THIS AND ALL MEDICATIONS OUT OF THE REACH OF CHILDREN.
Store at controlled room temperature 20° to 25°C (68° to 77°F). [See USP]. Protect from light and moisture and avoid excessive heat.

Menatrol™

Manufactured in the USA by:
PureTek Corporation
Panorama City, CA 91402
For questions or information
call toll-free: 877-921-7873